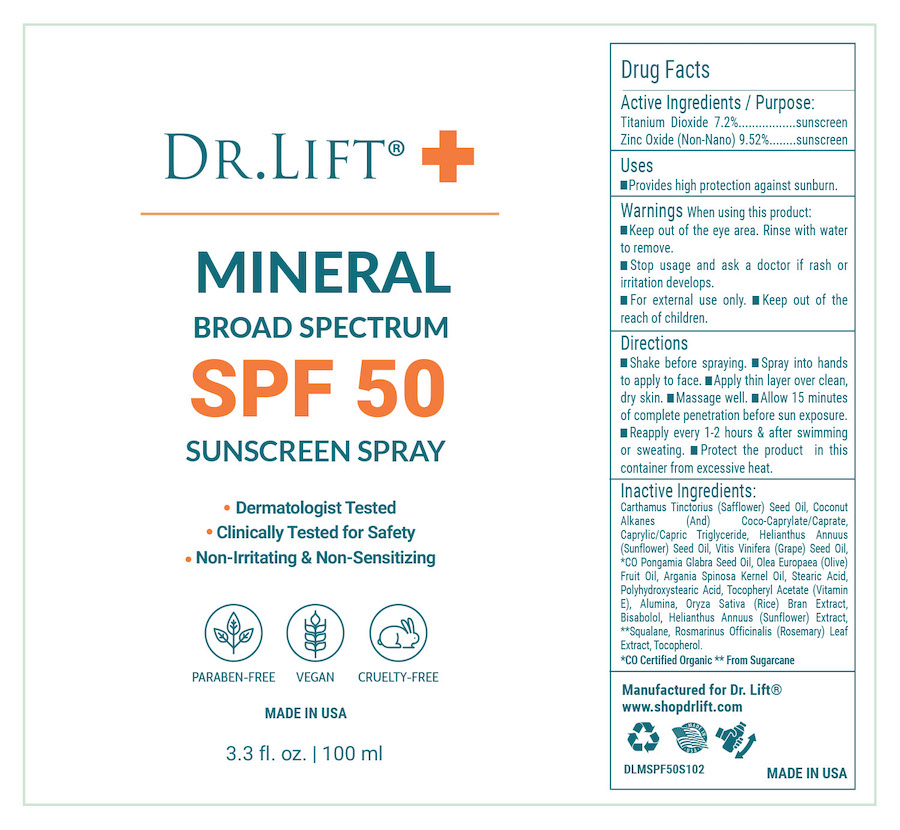 DRUG LABEL: Dr Lift Mineral SPF 50
NDC: 68062-8311 | Form: SPRAY
Manufacturer: Spa de Soleil
Category: otc | Type: HUMAN OTC DRUG LABEL
Date: 20251009

ACTIVE INGREDIENTS: TITANIUM DIOXIDE 72 mg/100 mL; ZINC OXIDE 952 mg/100 mL
INACTIVE INGREDIENTS: ALUMINA; ORYZA SATIVA (RICE) BRAN; STEARIC ACID; SQUALANE; POLYHYDROXYSTEARIC ACID (2300 MW); HELIANTHUS ANNUUS FLOWERING TOP; PONGAMIA GLABRA SEED OIL; ROSMARINUS OFFICINALIS (ROSEMARY) LEAF OIL; TOCOPHEROL; ALPHA-TOCOPHEROL ACETATE; CARTHAMUS TINCTORIUS (SAFFLOWER) SEED OIL; COCONUT ALKANES; COCO-CAPRYLATE/CAPRATE; CAPRYLIC/CAPRIC TRIGLYCERIDE; HELIANTHUS ANNUUS (SUNFLOWER) SEED OIL; VITIS VINIFERA (GRAPE) SEED OIL; OLEA EUROPAEA (OLIVE) FRUIT OIL; ARGANIA SPINOSA KERNEL OIL; BISABOLOL

Dr Lift Mineral SPF 50

Active Ingredients

Titanium Dioxide 7.2%

Zinc Oxide 9.52%

Purpose

Sunscreen

Warnings

WarningsWhen using this product

- keep out of the eye area
- rinse with water to remove
- stop use and ask a doctor if rash or irritation develops
- for external use onlyl
- keep out of reach of children

Keep out of reach of children.

Directions

Shake before spraying. Spray into hands to apply to face. Apply thin layer over clean, dry skin. Massage well. Allow 15 minutes of complete penetration before sun exposure. Reapply every 1-2 hours & after swimming or sweating. Protect the product in this container from excessive heat.

Uses
Provides high protection against sunburn.

Inactive Ingredients

Carthamus Tinctorius (Safflower) Seed Oil, Coconut Alkanes (And) Coco-Caprylate/Caprate, Caprylic/Capric Triglyceride, Helianthus Annuus (Sunflower) Seed Oil, Vitis Vinifera (Grape) Seed Oil, *CO Pongamia Glabra Seed Oil, Olea Europaea (Olive) Fruit Oil, Argania Spinosa Kernel Oil, Stearic Acid, Polyhydroxystearic Acid, Tocopheryl Acetate (Vitamin E), Alumina, Oryza Sativa (Rice) Bran Extract, Bisabolol, Helianthus Annuus (Sunflower) Extract, **Squalane, Rosmarinus Officinalis (Rosemary) Leaf Extract, Tocopherol.